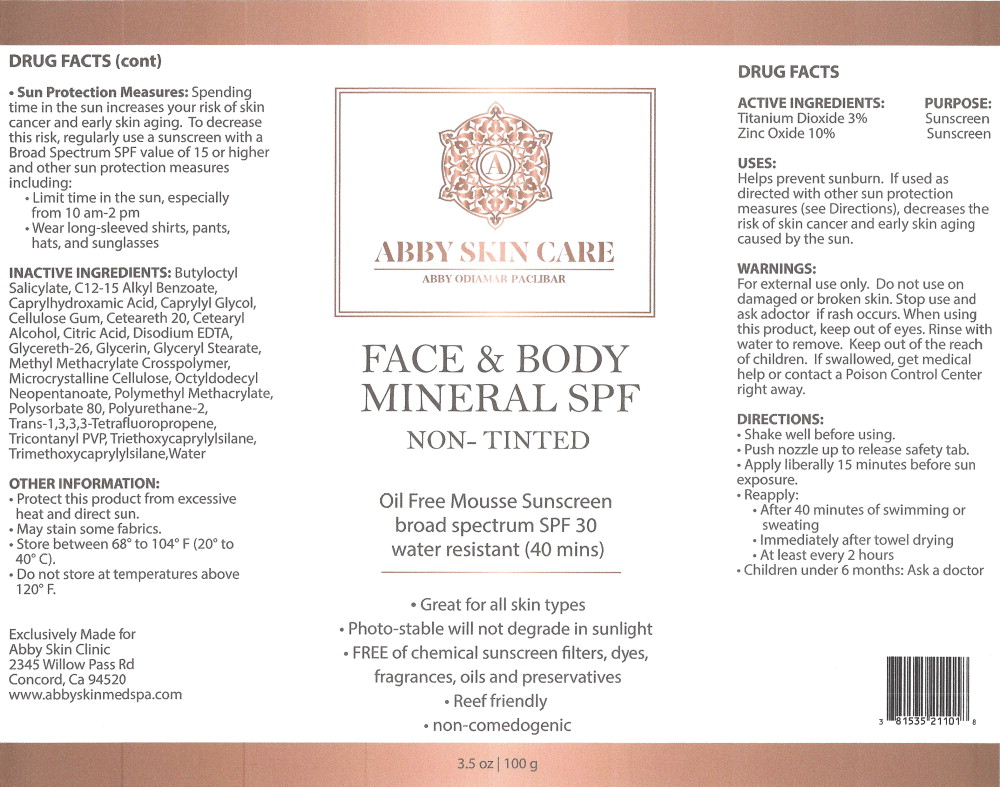 DRUG LABEL: Face and Body Mineral SPF Non-Tinted
NDC: 81535-211 | Form: AEROSOL, FOAM
Manufacturer: Flawless Skin Care, LLC (dba Abby Skin Clinic)
Category: otc | Type: HUMAN OTC DRUG LABEL
Date: 20210323

ACTIVE INGREDIENTS: Titanium Dioxide 30 mg/1 g; Zinc Oxide 100 mg/1 g
INACTIVE INGREDIENTS: BUTYLOCTYL SALICYLATE; ALKYL (C12-15) BENZOATE; CAPRYLHYDROXAMIC ACID; CAPRYLYL GLYCOL; CARBOXYMETHYLCELLULOSE SODIUM, UNSPECIFIED FORM; POLYOXYL 20 CETOSTEARYL ETHER; CETOSTEARYL ALCOHOL; CITRIC ACID MONOHYDRATE; EDETATE DISODIUM ANHYDROUS; GLYCERETH-26; GLYCERIN; GLYCERYL MONOSTEARATE; METHYL METHACRYLATE/GLYCOL DIMETHACRYLATE CROSSPOLYMER; MICROCRYSTALLINE CELLULOSE; OCTYLDODECYL NEOPENTANOATE; POLYHYDROXYSTEARIC ACID (2300 MW); POLY(METHYL METHACRYLATE; 450000 MW); POLYSORBATE 80; 1,3,3,3-TETRAFLUOROPROPENE, (1E)-; TRICONTANYL POVIDONE; TRIETHOXYCAPRYLYLSILANE; WATER

DRUG FACTS

ACTIVE INGREDIENTS:

Titanium Dioxide 3%

Zinc Oxide 10%

PURPOSE:

Sunscreen

Sunscreen

USES:

Helps prevent sunburn. If used as directed with other sun protection measures (see Directions), decreases the risk of skin cancer and early skin aging caused by the sun.

WARNINGS:

For external use only. Do not use on damaged or broken skin. Stop use and ask a doctor if rash occurs. When using this product, keep out of eyes. Rinse with water to remove. Keep out of the reach of children. If swallowed, get medical help or contact a Poison Control Center right away.

DIRECTIONS:

- Shake well before using.
- Push nozzle up to release safety tab.
- Apply liberally 15 minutes before sun exposure.
- Reapply:
  - After 40 minutes of swimming or sweating
  - Immediately after towel drying
  - At least every 2 hours
- Children under 6 months: Ask a doctor
- Sun Protection Measures: Spending time in the sun increases your risk of skin cancer and early skin aging. To decrease this risk, regularly use a sunscreen with a Broad Spectrum SPF value of 15 or higher and other sun protection measures including:
  - Limit time in the sun, especially from 10 am-2 pm
  - Wear long-sleeved shirts, pants, hats, and sunglasses

INACTIVE INGREDIENTS:

Butyloctyl Salicylate, Cl2-15 Alkyl Benzoate, Caprylhydroxamic Acid, Caprylyl Glycol, Cellulose Gum, Ceteareth 20, Cetearyl Alcohol, Citric Acid, Disodium EDTA, Glycereth-26, Glycerin, Glyceryl Stearate, Methyl Methacrylate Crosspolymer, Microcrystalline Cellulose, Octyldodecyl Neopentanoate, Polymethyl Methacrylate, Polysorbate 80, Polyurethane-2, Trans-1,3,3,3-Tetrafluoropropene, Tricontanyl PVP, Triethoxycaprylylsilane, Trimethoxycaprylylsilane, Water

OTHER INFORMATION:

- Protect this product from excessive heat and direct sun
- May stain some fabrics
- Store between 68° to 104° F (20° to 40° C).
- Do not store at temperatures above 120° F.

Principal Display Panel - 100 g Can Label

ABBY SKIN CARE

ABBY ODIAMAR PACLIBAR

FACE & BODY
MINERAL SPF
NON-TINTED

Oil Free Mousse Sunscreen
broad spectrum SPF 30
water resistant (40 mins)

- Great for all skin types
- Photo-stable will not degrade in sunlight
- FREE of chemical sunscreen filters, dyes,
  fragrances, oils and preservatives
- Reef friendly
- non-comedogenic

3.5 oz | 100 g